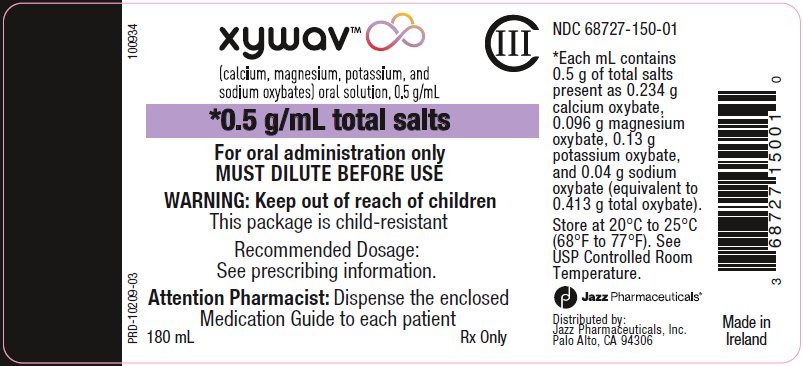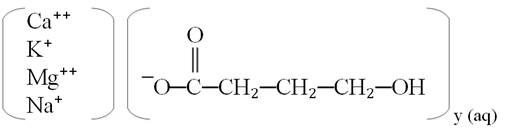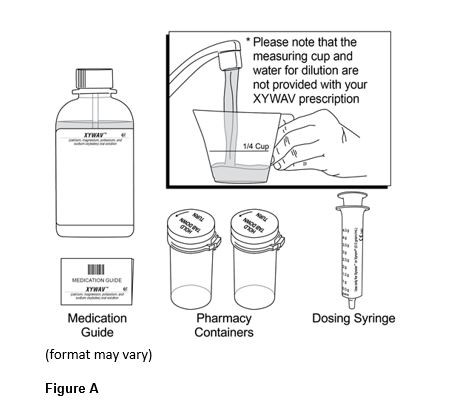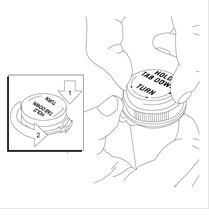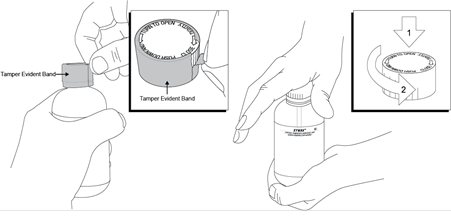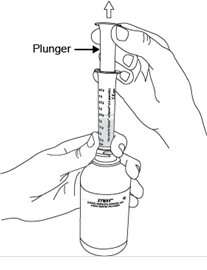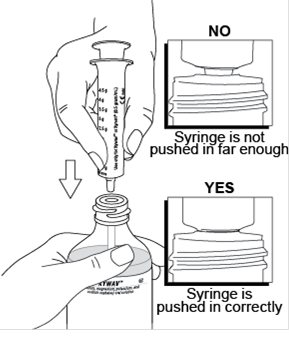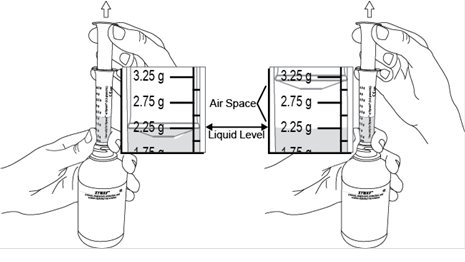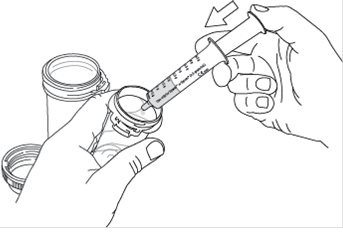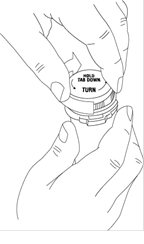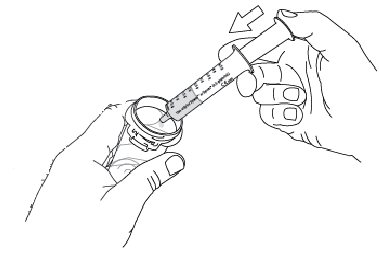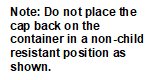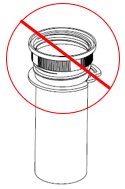 DRUG LABEL: XYWAV
NDC: 68727-150 | Form: SOLUTION
Manufacturer: Jazz Pharmaceuticals, Inc.
Category: prescription | Type: HUMAN PRESCRIPTION DRUG LABEL
Date: 20250701
DEA Schedule: CIII

ACTIVE INGREDIENTS: SODIUM OXYBATE 0.5 g/1 mL; Calcium Oxybate 0.5 g/1 mL; Potassium Oxybate 0.5 g/1 mL; Magnesium Oxybate 0.5 g/1 mL

HIGHLIGHTS OF PRESCRIBING INFORMATION

These highlights do not include all the information needed to use XYWAV safely and effectively. See full prescribing information for XYWAV.
XYWAV® (calcium, magnesium, potassium, and sodium oxybates) oral solution, CIII
Initial U.S. Approval: 2002

WARNING: CENTRAL NERVOUS SYSTEM DEPRESSION and ABUSE AND MISUSE.

WARNING: CENTRAL NERVOUS SYSTEM (CNS) DEPRESSION and ABUSE AND MISUSE.

See full prescribing information for complete boxed warning.

Central Nervous System Depression

- XYWAV is a CNS depressant, and respiratory depression can occur with XYWAV use (5.1, 5.4)

Abuse and Misuse

- The active moiety of XYWAV is oxybate or gamma-hydroxybutyrate (GHB). Abuse or misuse of illicit GHB is associated with CNS adverse reactions, including seizure, respiratory depression, decreased consciousness, coma, and death (5.2, 9.2)

XYWAV is available only through a restricted program called the XYWAV and XYREM REMS (5.3)

1 INDICATIONS AND USAGE

XYWAV is a central nervous system depressant indicated for the treatment of:

- Cataplexy or excessive daytime sleepiness (EDS) in patients 7 years of age and older with narcolepsy (1.1).
- Idiopathic Hypersomnia (IH) in adults (1.2).

2 DOSAGE AND ADMINISTRATION

See Full Prescribing Information for complete dosing instructions (2.1-2.7).

Dosage for Adult Patients with Narcolepsy

- Initiate dosage at 4.5 g per night orally, divided into two doses (2.1).
- Titrate to effect in increments of up to 1.5 g per night per week (2.1).
- Recommended dosage range: 6 g to 9 g per night orally, divided into two doses (2.1).
- Doses may be divided equally or unequally and the first dose taken at bedtime and the second dose taken 2.5 to 4 hours later (2.1).

Dosage for Pediatric Patients with Narcolepsy (7 Years of Age and Older)

- The recommended starting dosage, titration regimen, and maximum total nightly dosage are based on body weight (2.2).

Dosage for Adult Patients with Idiopathic Hypersomnia

- XYWAV can be administered as a twice or once nightly regimen in adults (2.3).
- Twice nightly: Initiate dosage at 4.5 g or less per night orally, divided into two doses. Titrate to effect in increments of up to 1.5 g per night per week, up to 9 g total nightly dose (2.3).
- Once nightly: Initiate dosage at 3 g or less per night orally, as one dose. Titrate to effect in increments of up to 1.5 g per night per week, up to 6 g total nightly dose (2.3).

Important Administration Information

- Administer XYWAV at least 2 hours after eating (2.4).
- Prepare XYWAV prior to bedtime; dilute with approximately ¼ cup of water in pharmacy-provided containers (2.4).
- Take XYWAV while in bed and lie down after dosing (2.4).

For Patients Transitioning from Xyrem to XYWAV: Initiate at the same dose and regimen as Xyrem (gram for gram). Titrate as needed based on efficacy and tolerability (2.5).

Patients with Hepatic Impairment

Recommended starting dosage is one-half of the original dosage per night administered orally, divided into two doses (2.6).

3 DOSAGE FORMS AND STRENGTHS

Oral solution: 0.5 g/mL total salts (equivalent to 0.413 g/mL of oxybate) (3)

4 CONTRAINDICATIONS

- In combination with sedative hypnotics or alcohol (4)
- Succinic semialdehyde dehydrogenase deficiency (4)

5 WARNINGS AND PRECAUTIONS

- CNS depression: Use caution when considering the concurrent use of XYWAV with other CNS depressants (5.1).
- Caution patients against hazardous activities requiring complete mental alertness or motor coordination within the first 6 hours of dosing or after first initiating treatment until certain that XYWAV does not affect them adversely (5.1).
- Depression and suicidality: Monitor patients for emergent or increased depression and suicidality (5.5).
- Confusion/Anxiety: Monitor for impaired motor/cognitive function (5.6).
- Parasomnias: Evaluate episodes of sleepwalking (5.7).

6 ADVERSE REACTIONS

Most common adverse reactions in adults with narcolepsy or IH (≥5%) were nausea, headache, dizziness, anxiety, insomnia, decreased appetite, hyperhidrosis, vomiting, diarrhea, dry mouth, parasomnia, somnolence, fatigue, and tremor (6.1).
In a pediatric study with sodium oxybate (same active moiety as XYWAV), the most common adverse reactions (≥5%) were nausea, enuresis, vomiting, headache, weight decreased, decreased appetite, dizziness, and sleepwalking (6.1).
To report SUSPECTED ADVERSE REACTIONS, contact Jazz Pharmaceuticals, Inc. at 1-800-520-5568, or FDA at 1-800-FDA-1088 or www.fda.gov/Medwatch.

7 DRUG INTERACTIONS

- Concomitant use with divalproex sodium: An initial reduction in XYWAV dose of at least 20% is recommended (2.7, 7.2).

8 USE IN SPECIFIC POPULATIONS

- Pregnancy: Based on animal data, may cause fetal harm (8.1).
- Geriatric patients: Monitor for impaired motor and/or cognitive function when taking XYWAV (8.5).

FULL PRESCRIBING INFORMATION

WARNING: CENTRAL NERVOUS SYSTEM DEPRESSION and ABUSE AND MISUSE.

- Central Nervous System Depression
  XYWAV is a CNS depressant. Clinically significant respiratory depression and obtundation may occur in patients treated with XYWAV at recommended doses [see Warnings and Precautions (5.1, 5.4)]. Many patients who received XYWAV during clinical trials in narcolepsy and idiopathic hypersomnia were receiving central nervous system stimulants [see Clinical Studies (14.1, 14.2, 14.3)].
- Abuse and Misuse
  The active moiety of XYWAV is oxybate or gamma-hydroxybutyrate (GHB). Abuse or misuse of illicit GHB, either alone or in combination with other CNS depressants, is associated with CNS adverse reactions, including seizure, respiratory depression, decreases in the level of consciousness, coma, and death [see Warnings and Precautions (5.2)].
  Because of the risks of CNS depression and abuse and misuse, XYWAV is available only through a restricted program under a Risk Evaluation and Mitigation Strategy (REMS) called the XYWAV and XYREM REMS [see Warnings and Precautions (5.3)].

1 INDICATIONS AND USAGE

1.1 Narcolepsy

XYWAV is indicated for the treatment of cataplexy or excessive daytime sleepiness (EDS) in patients 7 years of age and older with narcolepsy.

1.2 Idiopathic Hypersomnia

XYWAV is indicated for the treatment of idiopathic hypersomnia (IH) in adults.

2 DOSAGE AND ADMINISTRATION

2.1 Dosing Information in Adult Patients with Narcolepsy

The recommended starting dosage is 4.5 grams (g) per night administered orally, divided into two doses: 2.25 g at bedtime and 2.25 g taken 2.5 to 4 hours later (see Table 1). Increase the dosage by up to 1.5 g per night per week (e.g., 0.75 g at bedtime and 0.75 g taken 2.5 to 4 hours later), to the recommended dosage range of 6 g to 9 g per night. The dosage may be gradually titrated based on efficacy and tolerability. Some patients may achieve better responses with unequal doses at bedtime and 2.5 to 4 hours later. Doses higher than 9 g per night have not been studied and ordinarily should not be administered.

Table 1: Recommended Adult XYWAV Dosage Regimen (g = grams)
If a Patient’s Total Nightly Dosage Is: | Take at Bedtime: | Take 2.5 to 4 Hours Later:
4.5 g per night | 2.25 g | 2.25 g
6 g per night | 3 g | 3 g
7.5 g per night | 3.75 g | 3.75 g
9 g per night | 4.5 g | 4.5 g
Note: Some patients may achieve better responses with unequal nightly doses at bedtime and 2.5 to 4 hours later.

2.2 Dosing Information in Pediatric Patients with Narcolepsy

For pediatric patients 7 years of age and older, XYWAV is administered orally twice per night. The recommended starting pediatric dosage, titration regimen, and maximum total nightly dosage are based on patient weight, as specified in Table 2. The dosage may be gradually titrated based on efficacy and tolerability. Doses higher than 9 g per night have not been studied and ordinarily should not be administered.

Table 2: Recommended XYWAV Dosage for Patients 7 Years of Age and Older*
Patient Weight | Initial Dosage |  | Maximum Weekly Dosage Increase |  | Maximum Recommended Dosage
Patient Weight | Take at Bedtime: | Take 2.5 to 4 Hours Later: | Take at Bedtime: | Take 2.5 to 4 Hours Later: | Take at Bedtime: | Take 2.5 to 4 Hours Later:
<20 kg** | There is insufficient information to provide specific dosing recommendations for patients who weigh less than 20 kg.
20 kg to <30 kg | ≤1 g | ≤1 g | 0.5 g | 0.5 g | 3 g | 3 g
30 kg to <45 kg | ≤1.5 g | ≤1.5 g | 0.5 g | 0.5 g | 3.75 g | 3.75 g
≥45 kg | ≤2.25 g | ≤2.25 g | 0.75 g | 0.75 g | 4.5 g | 4.5 g
* For patients who sleep more than 8 hours per night, the first nightly dose of XYWAV may be given at bedtime or after an initial period of sleep.
** If XYWAV is used in patients 7 years of age and older who weigh less than 20 kg, a lower starting dosage, lower maximum weekly dosage increases, and lower total maximum nightly dosage should be considered.
Note: Some patients may achieve better responses with unequal nightly doses at bedtime and 2.5 to 4 hours later.

2.3 Dosing Information in Adult Patients with Idiopathic Hypersomnia (IH)

The dosage and regimen of XYWAV should be individualized based on clinical presentation [see Clinical Studies (14.3)].

XYWAV can be administered as a twice nightly or once nightly regimen. The recommended starting dose, titration guidance, and maximum nightly doses appear in Table 3:

Table 3: Recommended Nightly Dosage in Adult Patients with IH
Dosing Regimen | Starting Nightly Dose | Titration Increments | Maximum Total Nightly Dose
Twice nightly*,† | ≤4.5 g per night divided into two doses (e.g., 2.25 g each) | ≤1.5 g per night per week (divided into two doses) | 9 g (divided into two doses)
Once nightly | ≤3 g per night | ≤1.5 g per night per week | 6 g
* Some patients may achieve better responses with unequal nightly doses at bedtime and 2.5 to 4 hours later.
† The first dose should be taken at bedtime and the second dose taken 2.5 to 4 hours later.

The increase in the total nightly dose should not exceed 1.5 g /week. During titration, the dosing regimen may be changed between twice nightly and once nightly, as needed based on efficacy and tolerability [see Clinical Studies (14.3)]. Doses higher than 9 g per night or single dose administrations higher than 6 g have not been studied and should not be administered.

2.4 Important Administration Instructions for All Patients

Administer XYWAV at least 2 hours after eating [see Clinical Pharmacology (12.3)]. Prepare all doses of XYWAV prior to bedtime. Prior to ingestion, each dose of XYWAV should be diluted with approximately ¼ cup (approximately 60 mL) of water in the empty pharmacy-provided containers. Solutions prepared following dilution should be consumed within 24 hours.

Patients should take each dose of XYWAV while in bed and lie down immediately after dosing, and remain in bed following ingestion of each dose. XYWAV may cause patients to fall asleep abruptly without first feeling drowsy [see Adverse Reactions (6.2)].

Patients will often fall asleep within 5 minutes of taking XYWAV, and will usually fall asleep within 15 minutes, though the time it takes any individual patient to fall asleep may vary from night to night.

If dosing twice nightly, patients may need to set an alarm to awaken for the second dose. If the second dose is missed, that dose should be skipped and XYWAV should not be taken again until the next night. Two XYWAV doses should never be taken at one time.

2.5 Patients Transitioning from Xyrem to XYWAV

On the first night of dosing with XYWAV, initiate treatment at the same dose (gram for gram) and regimen as Xyrem. Titrate as needed based on efficacy and tolerability [see Dosage and Administration (2.1)].

2.6 Dosage Modification in Patients with Hepatic Impairment

The recommended starting dosage in patients with hepatic impairment is one-half of the original dosage per night administered orally, divided into two doses [see Use in Specific Populations (8.6) and Clinical Pharmacology (12.3)].

2.7 Dosage Adjustment with Co-administration of Divalproex Sodium

When initiating divalproex sodium in patients taking a stable dosage of XYWAV, a reduction of the XYWAV dosage by at least 20% is recommended with initial concomitant use [see Drug Interactions (7.2) and Clinical Pharmacology (12.3)]. When initiating XYWAV in patients already taking divalproex sodium, a lower starting dosage of XYWAV is recommended. Subsequently, the dosage of XYWAV can be adjusted based on individual clinical response and tolerability.

3 DOSAGE FORMS AND STRENGTHS

XYWAV is a clear to slightly opalescent oral solution at a total salt concentration of 0.5 g per mL. Each mL contains 0.5 g of total salts present as 0.234 g calcium oxybate, 0.096 g magnesium oxybate, 0.13 g potassium oxybate, and 0.04 g sodium oxybate (equivalent to 0.413 g total oxybate).

4 CONTRAINDICATIONS

XYWAV is contraindicated for use in:

- combination with sedative hypnotics [see Warnings and Precautions (5.1)].
- combination with alcohol [see Warnings and Precautions (5.1, 5.2)].
- patients with succinic semialdehyde dehydrogenase deficiency [see Clinical Pharmacology (12.3)].

5 WARNINGS AND PRECAUTIONS

5.1 Central Nervous System Depression

XYWAV is a central nervous system (CNS) depressant. Clinically significant respiratory depression and obtundation has occurred in adult patients taking sodium oxybate (same active moiety as XYWAV) at recommended doses in clinical trials and may occur in patients treated with XYWAV at recommended doses. XYWAV is contraindicated in combination with alcohol and sedative hypnotics. The concurrent use of XYWAV with other CNS depressants, including but not limited to opioid analgesics, benzodiazepines, sedating antidepressants or antipsychotics, sedating anti-epileptic drugs, general anesthetics, muscle relaxants, and/or illicit CNS depressants, may increase the risk of respiratory depression, hypotension, profound sedation, syncope, and death.

If use of these CNS depressants in combination with XYWAV is required, dose reduction or discontinuation of one or more CNS depressants (including XYWAV) should be considered. In addition, if short-term use of an opioid (e.g., post- or perioperative) is required, interruption of treatment with XYWAV should be considered.

Healthcare providers should caution patients about operating hazardous machinery, including automobiles or airplanes, until they are reasonably certain that XYWAV does not affect them adversely (e.g., impair judgment, thinking, or motor skills). Patients should not engage in hazardous occupations or activities requiring complete mental alertness or motor coordination, such as operating machinery or a motor vehicle or flying an airplane, for at least 6 hours after taking XYWAV. Patients should be queried about CNS depression‐related events upon initiation of XYWAV therapy and periodically thereafter.

XYWAV is available only through a restricted program under a REMS [see Warnings and Precautions (5.3)].

5.2 Abuse and Misuse

XYWAV is a Schedule III controlled substance. The active moiety of XYWAV is oxybate, also known as gamma-hydroxybutyrate (GHB), a Schedule I controlled substance. Abuse of illicit GHB, either alone or in combination with other CNS depressants, is associated with CNS adverse reactions, including seizure, respiratory depression, decreases in the level of consciousness, coma, and death. The rapid onset of sedation, coupled with the amnestic features of GHB, particularly when combined with alcohol, has proven to be dangerous for the voluntary and involuntary user (e.g., assault victim). Because illicit use and abuse of GHB have been reported, healthcare providers should carefully evaluate patients for a history of drug abuse and follow them closely, particularly for signs of misuse or abuse of GHB (including but not limited to increase in size or frequency of dosing, drug-seeking behavior, feigned cataplexy) [see Drug Abuse and Dependence (9.2)]. If abuse is suspected, treatment with XYWAV should be discontinued.

XYWAV is available only through a restricted program under a REMS [see Warnings and Precautions (5.3)].

5.3 XYWAV and XYREM REMS

XYWAV is available only through a restricted distribution program called the XYWAV and XYREM REMS because of the risks of central nervous system depression, and abuse and misuse [see Warnings and Precautions (5.1, 5.2)].

Notable requirements of the XYWAV and XYREM REMS include the following:

- Healthcare Providers who prescribe XYWAV are specially certified
- XYWAV will be dispensed only by the central pharmacy that is specially certified
- XYWAV will be dispensed and shipped only to patients who are enrolled in the XYWAV and XYREM REMS with documentation of safe use.

Further information is available at www.XYWAVXYREMREMS.com or 1-866-997-3688.

5.4 Respiratory Depression and Sleep-Disordered Breathing

XYWAV may impair respiratory drive, especially in patients with compromised respiratory function. In overdoses of oxybate and with illicit use of GHB, life-threatening respiratory depression has been reported [see Overdosage (10)].

Increased apnea and reduced oxygenation may occur with XYWAV administration in adult and pediatric patients. A significant increase in the number of central apneas and clinically significant oxygen desaturation may occur in patients with obstructive sleep apnea treated with XYWAV.

In a study assessing the respiratory-depressant effects of Xyrem (same active moiety as XYWAV) at doses up to 9 g per night in 21 adult patients with narcolepsy, no dose-related changes in oxygen saturation were demonstrated in the group as a whole. One of the four patients with preexisting moderate-to-severe sleep apnea had significant worsening of the apnea/hypopnea index during treatment.

In a study assessing the effects of Xyrem 9 g per night in 50 adult patients with obstructive sleep apnea, Xyrem did not increase the severity of sleep‑disordered breathing and did not adversely affect the average duration and severity of oxygen desaturation overall. However, there was a significant increase in the number of central apneas in patients taking Xyrem, and clinically significant oxygen desaturation (≤55%) was measured in three patients (6%) after Xyrem administration, with one patient withdrawing from the study and two continuing after single brief instances of desaturation.

During polysomnographic evaluation (PSG), central sleep apnea and oxygen desaturation were observed in pediatric patients with narcolepsy treated with Xyrem.

Prescribers should be aware that increased central apneas and clinically relevant oxygen desaturation events have been observed with sodium oxybate administration in adult and pediatric patients.

In clinical trials of Xyrem in 128 adult patients with narcolepsy, two patients had profound CNS depression, which resolved after supportive respiratory intervention. Two other patients discontinued sodium oxybate because of severe difficulty breathing and an increase in obstructive sleep apnea. In two controlled trials assessing PSG measures in adult patients with narcolepsy, 40 of 477 patients were included with a baseline apnea/hypopnea index of 16 to 67 events per hour, indicative of mild to severe sleep-disordered breathing. None of the 40 patients had a clinically significant worsening of respiratory function, as measured by apnea/hypopnea index and pulse oximetry at doses of 4.5 g to 9 g per night.

Prescribers should be aware that sleep-related breathing disorders tend to be more prevalent in obese patients, in men, in postmenopausal women not on hormone replacement therapy, and among patients with narcolepsy.

5.5 Depression and Suicidality

Depression, and suicidal ideation and behavior can occur in patients treated with XYWAV.

In Study 1 [see Clinical Studies (14.1)], depression and depressed mood were reported in 3% and 4%, respectively, of patients treated with XYWAV. Two patients (1%) discontinued XYWAV because of depression, but in most cases, no change in XYWAV treatment was required.

In Study 2 [see Clinical Studies (14.3)], depression and depressed mood were reported in 1 patient (1%) and in 5 patients (3%), respectively, of patients treated with XYWAV, all of whom continued XYWAV treatment.

In clinical trials of Xyrem (same active moiety as XYWAV) in adult patients with narcolepsy (n=781), there were two suicides and two attempted suicides in patients treated with Xyrem, including three patients with a previous history of depressive psychiatric disorder. Of the two suicides, one patient used Xyrem in conjunction with other drugs. Xyrem was not involved in the second suicide. Adverse reactions of depression were reported by 7% of 781 patients treated with Xyrem, with four patients (<1%) discontinuing because of depression. In most cases, no change in Xyrem treatment was required. In a clinical trial with Xyrem in pediatric patients with narcolepsy (n=104), one patient experienced suicidal ideation and two patients reported depression while taking Xyrem.

The emergence of depression in patients treated with XYWAV requires careful and immediate evaluation. Patients with a previous history of a depressive illness and/or suicide attempt should be monitored carefully for the emergence of depressive symptoms while taking XYWAV.

5.6 Other Behavioral or Psychiatric Adverse Reactions

Other behavioral and psychiatric adverse reactions can occur in patients taking XYWAV.

In Study 1, confusion occurred in 1% of patients treated with XYWAV and anxiety occurred in 5% of patients treated with XYWAV. One patient experienced visual hallucinations and confusion after ingesting approximately 9 grams of XYWAV.

In Study 2, confusion occurred in 3% of patients treated with XYWAV, and anxiety occurred in 16% patients treated with XYWAV. One patient experienced visual hallucinations which led to discontinuation of XYWAV.

Other neuropsychiatric reactions reported in clinical trials of Xyrem (same active moiety as XYWAV) in adult patients with narcolepsy and in the postmarketing setting included hallucinations, paranoia, psychosis, aggression, and agitation.

In a pediatric clinical trial with Xyrem in patients with narcolepsy, neuropsychiatric reactions, including acute psychosis, confusion, and anxiety, were reported while taking Xyrem.

The emergence or increase in the occurrence of behavioral or psychiatric events in patients taking XYWAV should be carefully monitored.

5.7 Parasomnias

Parasomnias can occur in patients taking XYWAV.

In Study 1, parasomnias, including sleepwalking, were reported in 6% of patients treated with XYWAV.

In Study 2, parasomnias, including sleepwalking, were reported in 5% of patients treated with XYWAV.

In a clinical trial of Xyrem (same active moiety as XYWAV) in adult patients with narcolepsy, five instances of sleepwalking with potential injury or significant injury were reported. Parasomnias, including sleepwalking, also have been reported in a pediatric clinical trial with sodium oxybate and in postmarketing experience with sodium oxybate.

Episodes of sleepwalking should be fully evaluated and appropriate interventions considered.

6 ADVERSE REACTIONS

The following clinically significant adverse reactions appear in other sections of the labeling:

- CNS depression [see Warnings and Precautions (5.1)]
- Abuse and Misuse [see Warnings and Precautions (5.2)]
- Respiratory Depression and Sleep-Disordered Breathing [see Warnings and Precautions (5.4)]
- Depression and Suicidality [see Warnings and Precautions (5.5)]
- Other Behavioral or Psychiatric Adverse Reactions [see Warnings and Precautions (5.6)]
- Parasomnias [see Warnings and Precautions (5.7)]

6.1 Clinical Trials Experience

Because clinical trials are conducted under widely varying conditions, adverse reaction rates observed in the clinical trials of a drug cannot be directly compared to rates in the clinical trials of another drug and may not reflect the rates observed in clinical practice.

Adult Patients with Narcolepsy

The safety of XYWAV was evaluated in a 16‑week double-blind placebo-controlled randomized-withdrawal study in patients with narcolepsy with cataplexy (Study 1), which was followed by an open-label extension phase lasting 24 weeks [see Clinical Studies (14.1)]. Study 1 included an open‑label titration period (OL OTTP), a stable-dose period (SDP), and a double‑blind, placebo‑controlled, randomized-withdrawal period (DB RWP). A total of 201 patients, ages 18 to 70 years, received XYWAV at individually titrated doses for 14 weeks, followed by randomization to XYWAV or matching placebo for 2 weeks of treatment. The mean exposure to XYWAV during this study, including titration, the randomized withdrawal period, and the open-label extension, was 151 days. In patients who remained on treatment, adverse reactions tended to occur early and diminish over time.

Adverse Reactions Leading to Treatment Discontinuation in Study 1

In Study 1, 9 of 201 patients (4%) reported adverse reactions that led to withdrawal from the study (anxiety, decreased appetite, depressed mood, depression, fatigue, headache, irritability, nausea, pain in extremity, parasomnia, somnolence, and vomiting). The most common adverse reaction leading to discontinuation was nausea (1.5%). The majority of adverse reactions leading to discontinuation began during the first few weeks of treatment.

Commonly Observed Adverse Reactions

The most common adverse reactions in Study 1 (incidence ≥5% of XYWAV-treated patients) were headache, nausea, dizziness, decreased appetite, parasomnia, diarrhea, hyperhidrosis, anxiety, and vomiting.

Adverse Reactions Occurring at an Incidence of 2% or Greater:

Table 4 lists adverse reactions observed in the open-label titration and stable dose periods of Study 1 that occurred at a frequency of 2% or greater in adult patients treated with XYWAV.

Table 4: Adverse Reactions Occurring in ≥2% of Adult Patients Treated with XYWAV in the Open-Label Titration and Stable Dose Periods in Study 1*
Adverse Reaction | Open-Label Titration Period + Stable Dose Period (14 weeks) (N=201) %
Headache | 20
Nausea | 13
Dizziness | 10
Decreased appetite | 8
Parasomnia† | 6
Diarrhea | 6
Hyperhidrosis‡ | 6
Anxiety§ | 5
Vomiting | 5
Fatigue¶ | 4
Dry mouth | 4
Depressed mood | 4
Enuresis | 4
Irritability | 3
Paresthesia | 3
Depression | 3
Tremor | 3
Somnolence | 2
Muscle spasms | 2
*Adverse reactions related to XYWAV were reported less frequently, as an overall incidence, in patients on Xyrem at study entry than in Xyrem-naïve patients.
†Includes abnormal dreams, abnormal sleep-related event, rapid eye movements sleep abnormal, sleep paralysis, sleep talking, sleep terror, sleep-related eating disorder, somnambulism
‡Includes hyperhidrosis and night sweats
§Includes anxiety, agitation, panic attack, tension
¶Includes fatigue and asthenia

Pediatric Patients (7 Years of Age and Older) with Narcolepsy

In the pediatric clinical trial with Xyrem (same active moiety as XYWAV), 104 patients aged 7 to 17 years (37 patients aged 7 to 11 years; 67 patients aged 12 to 17 years) with narcolepsy received Xyrem for up to one year [see Clinical Studies (14.2)]. This study included an open-label safety continuation period in which eligible patients received Xyrem for up to an additional 2 years. The median and maximum exposure across the entire study were 371 and 987 days, respectively.

Adverse Reactions Leading to Treatment Discontinuation

In the pediatric clinical trial with Xyrem, 7 of 104 patients reported adverse reactions that led to withdrawal from the study (hallucination, tactile; suicidal ideation; weight decreased; sleep apnea syndrome; affect lability; anger, anxiety, depression; and headache).

Adverse Reactions in the Xyrem Pediatric Clinical Trial

The most common adverse reactions (≥5%) were nausea (20%), enuresis (19%), vomiting (18%), headache (17%), weight decreased (13%), decreased appetite (9%), dizziness (8%), and sleepwalking (6%).

Additional information regarding safety in pediatric patients appears in the following sections:

- Respiratory Depression and Sleep-Disordered Breathing [see Warnings and Precautions (5.4)]
- Depression and Suicidality [see Warnings and Precautions (5.5)]
- Other Behavioral or Psychiatric Adverse Reactions [see Warnings and Precautions (5.6)]
- Parasomnias [see Warnings and Precautions (5.7)]

The overall adverse reaction profile of Xyrem in the pediatric clinical trial was similar to that seen in the adult clinical trial program. The safety profile in pediatric patients with XYWAV is expected to be similar to that of adult patients treated with XYWAV and to that of pediatric patients treated with Xyrem.

Adult Patients with Idiopathic Hypersomnia

The safety of XYWAV was evaluated in a double-blind placebo-controlled randomized‑withdrawal study in patients with IH (Study 2). This study consisted of an open‑label titration period (OL OTTP) up to 14 weeks, a stable-dose period (SDP) for 2 weeks, a double‑blind, placebo‑controlled, randomized-withdrawal period (DB RWP) for 2 weeks, and an open-label extension period for 24 weeks (all study periods up to 42 weeks) [see Clinical Studies (14.3)]. The study was conducted in 154 adult male and female patients ages 19 to 75 years of age with IH. The mean exposure to XYWAV during this study, including titration, the randomized withdrawal period, and the open-label extension, was 204 days. In patients who remained on treatment, adverse reactions tended to occur early and diminish over time.

Adverse Reactions Leading to Treatment Discontinuation in Study 2

In Study 2, across all study periods (excluding placebo during the DB RWP) (up to 42 weeks), 17 of 154 patients (11%) reported adverse reactions that led to withdrawal from the study (anxiety, nausea, insomnia, vomiting, fatigue, feeling abnormal, fall, decreased appetite, dizziness, paresthesia, tremor, parasomnia, confusional state, hallucination visual, and irritability). The most common adverse reaction leading to discontinuation was anxiety (3.2%). The majority of adverse reactions leading to discontinuation began during the first few weeks of treatment.

Commonly Observed Adverse Reactions

The most common adverse reactions in Study 2 (incidence ≥5% of XYWAV‑treated patients) in addition to those observed in Study 1 as most common were insomnia, dry mouth, fatigue, somnolence, and tremor.

The safety profile observed in Study 2 was similar to that of Study 1. Adverse reactions occurring in ≥2% of patients treated with XYWAV in the open-label titration and stable dose periods in Study 2 are shown in Table 5:

Table 5: Adverse Reactions Occurring in ≥2% of Patients Treated with XYWAV in the Open-Label Titration and Stable Dose Periods in Study 2
Adverse Reaction | Open-Label Titration Period + Stable Dose Period; (up to 16 weeks); (N=154); %
Nausea | 21
Headache | 16
Anxiety* | 12
Dizziness | 12
Insomnia† | 9
Hyperhidrosis‡ | 8
Decreased appetite | 8
Vomiting | 7
Dry mouth | 6
Diarrhea | 5
Fatigue§ | 5
Somnolence¶ | 5
Tremor | 5
Parasomnia# | 5
Balance disorder♠ | 3
Muscle spasms | 3
Fall | 3
Paresthesia | 3
Snoring | 3
Weight decreased | 3
Bruxism | 3
Confusional state | 3
Depressed mood | 3
Feeling drunk | 3
Irritability | 3
* includes anxiety, nervousness, and panic attack
† includes middle insomnia, initial insomnia, insomnia, and terminal insomnia
‡ includes hyperhidrosis and night sweats
§ includes fatigue and asthenia
¶ includes somnolence and sedation
# includes confusional arousal, sleep paralysis, nightmare, sleep talking, somnambulism, and
hypnopompic hallucination
♠ includes balance disorder and ataxia

Additional Adverse Reactions

Adverse reactions observed in clinical studies with Xyrem (≥2%), but not observed in Study 1 or Study 2 at a frequency of higher than 2%, and which may be relevant for XYWAV:

Pain, pain in extremity, cataplexy, disturbance in attention, sleep paralysis, and disorientation.

6.2 Postmarketing Experience

The following adverse reactions have been identified during postapproval use of sodium oxybate. Because these reactions are reported voluntarily from a population of uncertain size, it is not always possible to reliably estimate their frequency or establish a causal relationship to drug exposure:

Arthralgia, fall*, fluid retention, hangover, hypersensitivity, hypertension, memory impairment, nocturia, and vision blurred.
* The sudden onset of sleep in patients taking sodium oxybate, including in a standing position or while rising from bed, has led to falls complicated by injuries, in some cases requiring hospitalization.

7 DRUG INTERACTIONS

7.1 Alcohol, Sedative Hypnotics, and CNS Depressants

XYWAV is contraindicated for use in combination with alcohol or sedative hypnotics. Use of other CNS depressants may potentiate the CNS-depressant effects of XYWAV [see Warnings and Precautions (5.1)].

7.2 Divalproex Sodium

Concomitant use of sodium oxybate with divalproex sodium results in an increase in systemic exposure to GHB, which was shown to cause a greater impairment on some tests of attention and working memory in a clinical study [see Clinical Pharmacology (12.3)]. A similar increase in exposure is expected with concomitant use of XYWAV and divalproex sodium; therefore, an initial dose reduction of XYWAV is recommended when used concomitantly with divalproex sodium [see Dosage and Administration (2.7)]. Prescribers are advised to monitor patient response closely and adjust dose accordingly if concomitant use of XYWAV and divalproex sodium is warranted.

8 USE IN SPECIFIC POPULATIONS

8.1 Pregnancy

Risk Summary

There are no adequate data on the developmental risk associated with the use of XYWAV or sodium oxybate in pregnant women. Oral administration of sodium oxybate to pregnant rats (0, 150, 350, or 1,000 mg/kg/day) or rabbits (0, 300, 600, or 1,200 mg/kg/day) throughout organogenesis produced no clear evidence of developmental toxicity; however, oral administration to rats throughout pregnancy and lactation resulted in increased stillbirths and decreased offspring postnatal viability and growth, at a clinically relevant dose [see Data].

In the U.S. general population, the estimated background risk of major birth defects and miscarriage in clinically recognized pregnancies is 2-4% and 15-20%, respectively. The background risk of major birth defects and miscarriage for the indicated population is unknown.

Clinical Considerations

Labor or Delivery

XYWAV has not been studied in labor or delivery. In obstetric anesthesia using an injectable formulation of sodium oxybate, newborns had stable cardiovascular and respiratory measures but were very sleepy, causing a slight decrease in Apgar scores. There was a fall in the rate of uterine contractions 20 minutes after injection. Placental transfer is rapid, and gamma-hydroxybutyrate (GHB) has been detected in newborns at delivery after intravenous administration of GHB to mothers. Subsequent effects of sodium oxybate on later growth, development, and maturation in humans are unknown.

Data

Animal Data

Oral administration of sodium oxybate to pregnant rats (0, 150, 350, or 1,000 mg/kg/day) or rabbits (0, 300, 600, or 1,200 mg/kg/day) throughout organogenesis produced no clear evidence of developmental toxicity. The highest doses of sodium oxybate tested in rats and rabbits were approximately 1 and 3 times, respectively, the maximum recommended human dose (MRHD) of 9 g per night on a body surface area (mg/m^2) basis.

Additionally, oral administration of sodium oxybate (0, 150, 350, or 1,000 mg/kg/day) to rats throughout pregnancy and lactation resulted in increased stillbirths and decreased offspring postnatal viability and body weight gain at the highest dose tested. The no-effect dose for pre- and post-natal developmental toxicity in rats is less than the MRHD on a mg/m^2 basis.

8.2 Lactation

Risk Summary

GHB is excreted in human milk after oral administration of sodium oxybate. There is insufficient information on the risk to a breastfed infant, and there is insufficient information on milk production in nursing mothers. The developmental and health benefits of breastfeeding should be considered along with the mother's clinical need for XYWAV and any potential adverse effects on the breastfed infant from XYWAV or from the underlying maternal condition.

8.4 Pediatric Use

Narcolepsy

The safety and effectiveness of XYWAV for the treatment of cataplexy or excessive daytime sleepiness in pediatric patients 7 years of age and older with narcolepsy have been established. XYWAV has not been studied in a pediatric clinical trial. Use of XYWAV in pediatric patients 7 years of age and older with narcolepsy is supported by evidence from an adequate and well-controlled study of sodium oxybate in pediatric patients 7 to 17 years of age, a study in adults showing a treatment effect of XYWAV similar to that observed with sodium oxybate, pharmacokinetic data of sodium oxybate from adult and pediatric patients, and pharmacokinetic data of XYWAV from healthy adult volunteers [see Adverse Reactions (6.1) and Clinical Studies (14.1, 14.2)].

In the pediatric clinical trial with sodium oxybate administration in patients with narcolepsy, serious adverse reactions of central sleep apnea and oxygen desaturation documented by polysomnography evaluation; depression; suicidal ideation; neuropsychiatric reactions including acute psychosis, confusion, and anxiety; and parasomnias, including sleepwalking, have been reported [see Warnings and Precautions (5.4, 5.5, 5.6, 5.7) and Adverse Reactions (6.1)].

Safety and effectiveness of XYWAV for the treatment of cataplexy or excessive daytime sleepiness in pediatric patients below the age of 7 years have not been established.

Idiopathic Hypersomnia

Safety and effectiveness of XYWAV for the treatment of idiopathic hypersomnia in pediatric patients have not been established.

Juvenile Animal Toxicity Data

In a study in which sodium oxybate (0, 100, 300, or 900 mg/kg/day) was orally administered to rats during the juvenile period of development (postnatal days 21 through 90), mortality was observed at the two highest doses tested. Deaths occurred during the first week of dosing and were associated with clinical signs (including decreased activity and respiratory rate) consistent with the pharmacological effects of the drug. Reduced body weight gain in males and females and delayed sexual maturation in males were observed at the highest dose tested. The no-effect dose for adverse effects in juvenile rats is associated with plasma exposures (AUC) less than that at the maximum recommended human dose (9 g/night).

8.5 Geriatric Use

Clinical studies of XYWAV or Xyrem in patients with narcolepsy or IH did not include sufficient numbers of subjects age 65 years and older to determine whether they respond differently from younger subjects.

In clinical studies of sodium oxybate in another population, 39 (5%) of 874 patients were 65 years or older. Discontinuations of treatment due to adverse reactions were increased in the elderly compared to younger adults (21% vs. 19%). Frequency of headaches was markedly increased in the elderly (39% vs. 19%). The most common adverse reactions were similar in both age categories. In general, dose selection for an elderly patient should be cautious, usually starting at the low end of the dosing range, reflecting the greater frequency of decreased hepatic, renal, or cardiac function, and of concomitant disease or other drug therapy.

8.6 Hepatic Impairment

Because of an increase in exposure to XYWAV, the starting dose should be reduced by half in patients with hepatic impairment [see Dosage and Administration (2.6) and Clinical Pharmacology (12.3)].

9 DRUG ABUSE AND DEPENDENCE

9.1 Controlled Substance

XYWAV is a Schedule III controlled substance under the Federal Controlled Substances Act. Non-medical use of XYWAV could lead to penalties assessed under the higher Schedule I controls.

9.2 Abuse

The active moiety of XYWAV, oxybate, produces dose-dependent central nervous system effects, including hypnotic and positive subjective reinforcing effects. The onset of effect is rapid, enhancing its potential for abuse or misuse.

Drug abuse is the intentional non-therapeutic use of a drug product or substance, even once, for its desirable psychological or physiological effects. Misuse is the intentional use, for therapeutic purposes of a drug by an individual in a way other than prescribed by a health care provider or for whom it was not prescribed. Drug misuse and abuse may occur with or without progression to addiction. Drug addiction is a cluster of behavioral, cognitive, and physiological phenomena that may include a strong desire to take the drug, difficulties in controlling drug use (e.g., continuing drug use despite harmful consequences, giving a higher priority to drug use than other activities and obligations), and possible tolerance or physical dependence.

The rapid onset of sedation, coupled with the amnestic features of GHB, particularly when combined with alcohol, has proven to be dangerous for the voluntary and involuntary user (e.g., assault victim).

Illicit GHB is abused in social settings primarily by young adults. Some of the doses estimated to be abused are in a similar dosage range to that used for treatment of patients with cataplexy. GHB has some commonalities with ethanol over a limited dose range, and some cross tolerance with ethanol has been reported as well. Cases of severe dependence and craving for GHB have been reported when the drug is taken around the clock. Patterns of abuse indicative of dependence include: 1) the use of increasingly large doses, 2) increased frequency of use, and 3) continued use despite adverse consequences.

Because illicit use and abuse of GHB have been reported, physicians should carefully evaluate patients for a history of drug abuse and follow such patients closely, observing them for signs of misuse or abuse of GHB (e.g., increase in size or frequency of dosing, drug-seeking behavior, feigned cataplexy). Dispose of XYWAV according to state and federal regulations. It is safe to dispose of XYWAV down the sanitary sewer.

9.3 Dependence

Dependence

Physical dependence is a state that develops as a result of physiological adaptation in response to repeated drug use, manifested by withdrawal signs and symptoms after abrupt discontinuation or a significant dose reduction of a drug. There have been case reports of withdrawal, ranging from mild to severe, following discontinuation of illicit use of GHB at frequent repeated doses (18 g to 250 g per day) in excess of the recommended dosage range. Signs and symptoms of GHB withdrawal following abrupt discontinuation included insomnia, restlessness, anxiety, psychosis, lethargy, nausea, tremor, sweating, muscle cramps, tachycardia, headache, dizziness, rebound fatigue and sleepiness, confusion, and, particularly in the case of severe withdrawal, visual hallucinations, agitation, and delirium. These symptoms generally abated in 3 to 14 days. In cases of severe withdrawal, hospitalization may be required. In the clinical trial experience with Xyrem in narcolepsy/cataplexy patients at recommended doses, two patients reported anxiety and one reported insomnia following abrupt discontinuation at the termination of the clinical trial; in the two patients with anxiety, the frequency of cataplexy had increased markedly at the same time. In the XYWAV clinical trial in adult narcolepsy/cataplexy patients at recommended doses, one patient reported insomnia following abrupt discontinuation of XYWAV. In the XYWAV clinical trial in adult idiopathic hypersomnia patients at recommended doses, six patients reported insomnia, two patients reported early insomnia, and one patient reported visual and auditory hallucinations following abrupt discontinuation of XYWAV.

Tolerance

Tolerance is a physiological state characterized by a reduced response to a drug after repeated administration (i.e., a higher dose of a drug is required to produce the same effect that was once obtained at a lower dose). Tolerance to XYWAV has not been systematically studied in controlled clinical trials. There have been some case reports of symptoms of tolerance developing after illicit use at dosages far in excess of the recommended XYWAV dosage regimen. Clinical studies of sodium oxybate in the treatment of alcohol withdrawal suggest a potential cross-tolerance with alcohol. The safety and effectiveness of XYWAV in the treatment of alcohol withdrawal have not been established.

10 OVERDOSAGE

10.1 Human Experience

Information regarding overdose with XYWAV is derived largely from reports in the medical literature that describe symptoms and signs in individuals who have ingested GHB illicitly. In these circumstances the co-ingestion of other drugs and alcohol was common, and may have influenced the presentation and severity of clinical manifestations of overdose.

In adult clinical trials with Xyrem (same active moiety as XYWAV), two cases of overdose were reported. In the first case, an estimated dose of 150 g, more than 15 times the maximum recommended dose, caused a patient to be unresponsive with brief periods of apnea and to be incontinent of urine and feces. This individual recovered without sequelae. In the second case, death was reported following a multiple drug overdose consisting of Xyrem and numerous other drugs. No cases of overdose (greater than 9 g) with XYWAV were reported in the XYWAV clinical trials.

10.2 Signs and Symptoms

Information about signs and symptoms associated with overdosage with XYWAV derives from reports of illicit use of GHB. Patient presentation following overdose is influenced by the dose ingested, the time since ingestion, the co-ingestion of other drugs and alcohol, and the fed or fasted state. Patients have exhibited varying degrees of depressed consciousness that may fluctuate rapidly between a confusional, agitated combative state with ataxia and coma. Emesis (even when obtunded), diaphoresis, headache, and impaired psychomotor skills have been observed. No typical pupillary changes have been described to assist in diagnosis; pupillary reactivity to light is maintained. Blurred vision has been reported. An increasing depth of coma and acidosis have been observed at higher doses. Myoclonus and tonic-clonic seizures have been reported. Respiration may be unaffected or compromised in rate and depth. Cheyne-Stokes respiration and apnea have been observed. Bradycardia and hypothermia may accompany unconsciousness, as well as muscular hypotonia, but tendon reflexes remain intact.

10.3 Recommended Treatment of Overdose

General symptomatic and supportive care should be instituted immediately, and gastric decontamination may be considered if co-ingestants are suspected. Because emesis may occur in the presence of obtundation, appropriate posture (left lateral recumbent position) and protection of the airway by intubation may be warranted. Although the gag reflex may be absent in deeply comatose patients, even unconscious patients may become combative to intubation, and rapid-sequence induction (without the use of sedative) should be considered. Vital signs and consciousness should be closely monitored. The bradycardia reported with GHB overdose has been responsive to atropine intravenous administration. No reversal of the central depressant effects of XYWAV can be expected from naloxone or flumazenil administration. The use of hemodialysis and other forms of extracorporeal drug removal have not been studied in GHB overdose, but have been reported in cases of acidosis associated with GHB ingestions of 125 g or greater; however, due to the rapid metabolism of oxybate, these measures may not be warranted.

10.4 Poison Control Center

As with the management of all cases of drug overdosage, the possibility of multiple drug ingestion should be considered. The healthcare provider is encouraged to collect urine and blood samples for routine toxicologic screening, and to consult with a regional poison control center (1-800-222-1222) for current treatment recommendations.

11 DESCRIPTION

XYWAV oral solution contains oxybate, a CNS depressant. The chemical name of oxybate is gamma-hydroxybutyrate (GHB). XYWAV contains a mixture of calcium oxybate, magnesium oxybate, potassium oxybate, and sodium oxybate equivalent to 0.5 g/mL, which corresponds to 0.413 g/mL oxybate.

Each mL of XYWAV contains: 0.234 g calcium oxybate, Ca(C4H7O3)2; 0.096 g magnesium oxybate, Mg(C4H7O3)2; 0.13 g potassium oxybate, K(C4H7O3); and 0.04 g sodium oxybate, Na(C4H7O3) in dissociated form in the solution. The molecular weights of each are as follows: calcium oxybate is 246.3, magnesium oxybate is 230.5, potassium oxybate is 142.2, and sodium oxybate is 126.1.

The chemical structure is:

y=1 for Na^+ and K^+; y=2 for Mg^2+ and Ca^2+

The inactive ingredients are purified water and sucralose.
XYWAV contains no ingredient made from a gluten‑containing grain (wheat, barley, or rye).

12 CLINICAL PHARMACOLOGY

12.1 Mechanism of Action

XYWAV is a CNS depressant. The exact mechanism of action of XYWAV in the treatment of narcolepsy and idiopathic hypersomnia is unknown. XYWAV is a mixture of calcium oxybate, magnesium oxybate, potassium oxybate, and sodium oxybate (gamma-hydroxybutyrate). Gamma-hydroxybutyrate (GHB) is an endogenous compound and metabolite of the neurotransmitter GABA. It is hypothesized that the therapeutic effects of XYWAV are mediated through GABAB actions during sleep at noradrenergic and dopaminergic neurons, as well as at thalamocortical neurons.

12.3 Pharmacokinetics

Pharmacokinetics of GHB are nonlinear and are similar following single or repeat dosing. The pharmacokinetics of oxybate following administration of XYWAV are similar between healthy subjects and patients with narcolepsy or patients with idiopathic hypersomnia.

Absorption

Following oral administration of XYWAV, the average time to peak plasma concentration (Tmax) was about 1.3 hours in healthy adults in the fasted state.

Following oral administration of XYWAV, the plasma levels of GHB increased more than dose‑proportionally, with Cmax increasing approximately 2‐fold and AUC increasing 2.9-fold as the dose was doubled from 2.25 g to 4.5 g.

Effect of Food

Administration of XYWAV immediately after a high-fat meal resulted in a mean reduction in Cmax of GHB by 33%, and mean reduction in systemic exposure (AUC) by 16% [see Dosage and Administration (2.4)].

Distribution

GHB has an apparent volume of distribution averaging 190 mL/kg to 384 mL/kg. At GHB concentrations ranging from 3 mcg/mL to 300 mcg/mL. Less than 1% is bound to plasma proteins.

Elimination

Metabolism

Animal studies indicate that metabolism is the major elimination pathway for GHB, producing carbon dioxide and water via the tricarboxylic acid (Krebs) cycle and secondarily by beta-oxidation. The primary pathway involves a cytosolic NADP^+-linked enzyme, GHB dehydrogenase, that catalyzes the conversion of GHB to succinic semialdehyde, which is then biotransformed to succinic acid by the enzyme succinic semialdehyde dehydrogenase. Succinic acid enters the Krebs cycle where it is metabolized to carbon dioxide and water. A second mitochondrial oxidoreductase enzyme, a transhydrogenase, also catalyzes the conversion to succinic semialdehyde in the presence of α-ketoglutarate. An alternate pathway of biotransformation involves β-oxidation via 3,4-dihydroxybutyrate to carbon dioxide and water. No active metabolites have been identified.

Excretion

The clearance of GHB is almost entirely by biotransformation to carbon dioxide, which is then eliminated by expiration. On average, less than 5% of unchanged drug appears in human urine within 6 to 8 hours after dosing. Fecal excretion is negligible. GHB has a mean terminal elimination half-life of 0.66 hours.

Specific Populations

Geriatric Patients

There is limited experience with sodium oxybate and no experience with XYWAV in the elderly. Results from a pharmacokinetic study (n=20) in another studied population indicate that the pharmacokinetic characteristics of GHB are consistent among younger (ages 48 to 64 years) and older (ages 65 to 75 years) adults.

Pediatric Patients

The pharmacokinetics of XYWAV has not been directly evaluated in pediatric patients.

The pharmacokinetics of sodium oxybate was evaluated in pediatric patients aged 7 to 17 years and demonstrated similar PK properties as adults. A population pharmacokinetic model was developed with sodium oxybate data from pediatric and adult patients and healthy volunteers and with XYWAV data from healthy adult volunteers. The population PK model analyses demonstrate that body weight is the major intrinsic factor affecting GHB pharmacokinetics following sodium oxybate or XYWAV dosing. Additionally, XYWAV has similar PK characteristics (more than dose proportionality) as sodium oxybate in pediatric patients, supporting the same dose regimen as sodium oxybate and 1-to-1 dose switch from sodium oxybate to XYWAV in pediatric patients.

Male and Female Patients

In a study of 18 female and 18 male healthy adult volunteers, no gender differences were detected in the pharmacokinetics of GHB following a single Xyrem oral dose of 4.5 g.

Racial or Ethnic Groups

There are insufficient data to evaluate any pharmacokinetic differences among races.

Patients with Renal Impairment

No pharmacokinetic study in patients with renal impairment has been conducted.

Patients with Hepatic Impairment

The pharmacokinetics of GHB in 16 cirrhotic patients, half without ascites (Child’s Class A) and half with ascites (Child’s Class C), were compared to the kinetics in 8 subjects with normal hepatic function after a single sodium oxybate oral dose of 25 mg/kg. AUC values were double in the cirrhotic patients, with apparent oral clearance reduced from 9.1 mL/min/kg in healthy adults to 4.5 and 4.1 mL/min/kg in Class A and Class C patients, respectively. Elimination half-life was significantly longer in Class C and Class A patients than in control patients (mean t1/2 of 59 and 32 minutes, respectively, versus 22 minutes). The starting dose of XYWAV should be reduced in patients with hepatic impairment [see Dosage and Administration (2.6) and Use in Specific Populations (8.6)].

Drug Interactions Studies

Studies in vitro with pooled human liver microsomes indicate that sodium oxybate does not significantly inhibit the activities of the human isoenzymes CYP1A2, CYP2C9, CYP2C19, CYP2D6, CYP2E1, or CYP3A up to the concentration of 3 mM (378 mcg/mL), a level considerably higher than levels achieved with recommended doses.

Drug interaction studies in healthy adults (age 18 to 50 years) were conducted with sodium oxybate and divalproex sodium, diclofenac, and ibuprofen.

- Divalproex sodium: Co-administration of sodium oxybate (6 g per day as two equal doses of 3 grams dosed four hours apart) with divalproex sodium (valproic acid, 1250 mg per day) increased mean systemic exposure to GHB as shown by AUC by approximately 25% (AUC ratio range of 0.8 to 1.7), while Cmax was comparable. Co-administration did not appear to affect the pharmacokinetics of valproic acid. A greater impairment on some tests of attention and working memory was observed with co-administration of both drugs than with either drug alone [see Drug Interactions (7.2) and Dosage and Administration (2.7)].
- Diclofenac: Co-administration of sodium oxybate (6 g per day as two equal doses of 3 grams dosed four hours apart) with diclofenac (50 mg/dose twice per day) showed no significant differences in systemic exposure to GHB. Co-administration did not appear to affect the pharmacokinetics of diclofenac.
- Ibuprofen: Co-administration of sodium oxybate (6 g per day as two equal doses of 3 grams dosed four hours apart) with ibuprofen (800 mg/dose four times per day also dosed four hours apart) resulted in comparable systemic exposure to GHB as shown by plasma Cmax and AUC values. Co-administration did not affect the pharmacokinetics of ibuprofen.

Drug interaction studies in healthy adults demonstrated no pharmacokinetic interactions between sodium oxybate and protriptyline hydrochloride, zolpidem tartrate, and modafinil. Also, there were no pharmacokinetic interactions with the alcohol dehydrogenase inhibitor fomepizole. However, pharmacodynamic interactions with these drugs cannot be ruled out. Alteration of gastric pH with omeprazole produced no significant change in the pharmacokinetics of GHB. In addition, drug interaction studies in healthy adults demonstrated no pharmacokinetic or clinically significant pharmacodynamic interactions between sodium oxybate and duloxetine HCl.

13 NONCLINICAL TOXICOLOGY

13.1 Carcinogenesis, Mutagenesis, Impairment of Fertility

Carcinogenesis

Administration of sodium oxybate to rats at oral doses of up to 1,000 mg/kg/day for 83 (males) or 104 (females) weeks resulted in no increase in tumors. Plasma exposure (AUC) at the highest dose tested was 2 times that in humans at the maximum recommended human dose (MRHD) of 9 g per night.

The results of 2-year carcinogenicity studies in mouse and rat with gamma-butyrolactone, a compound that is metabolized to oxybate in vivo, showed no clear evidence of carcinogenic activity. The plasma AUCs of oxybate achieved at the highest doses tested in these studies were less than that in humans at the MRHD.

Mutagenesis

Sodium oxybate was negative in the in vitro bacterial gene mutation assay, an in vitro chromosomal aberration assay in mammalian cells, and in an in vivo rat micronucleus assay.

Impairment of Fertility

Oral administration of sodium oxybate (0, 150, 350, or 1,000 mg/kg/day) to male and female rats prior to and throughout mating and continuing in females through early gestation resulted in no adverse effects on fertility. The highest dose tested is approximately equal to the MRHD on a mg/m^2 basis.

14 CLINICAL STUDIES

14.1 Cataplexy and Excessive Daytime Sleepiness (EDS) in Adult Narcolepsy

Efficacy of XYWAV for the treatment of cataplexy and excessive daytime sleepiness in adult patients with narcolepsy was established in a double‑blind, placebo‑controlled, randomized‑withdrawal study (Study 1; NCT03030599). This study had two parts, consisting of the main study, followed by an optional 24-week open‑label extension (OLE). The main study consisted of a 12‑week open-label optimized treatment and titration period (OL OTTP), followed by a 2-week stable-dose period (SDP), and finally a 2‑week double-blind randomized-withdrawal period (DB RWP).

Study 1 enrolled 201 patients with narcolepsy with cataplexy, 18 to 70 years of age, with a baseline history of at least 14 cataplexy attacks in a typical 2-week period prior to any treatment for narcolepsy symptoms. Of the 201 patients, 134 were randomized 1:1 to continue treatment with XYWAV or to placebo in the 2‑week DB RWP. In the safety population, overall, the median age was 36.0 years (range: 18 to 70). The majority of subjects were female (61%), and most were white (88%) and not Hispanic or Latino (84%).

Patients entering the study were taking a stable dosage of 1) Xyrem only, 2) Xyrem + another anticataplectic, 3) a non-Xyrem anticataplectic, or 4) were cataplexy‑treatment naïve. Patients taking Xyrem at study entry were switched (at a gram for gram dose) from Xyrem to XYWAV for a minimum of 2 weeks and titrated, if needed, to a stable, tolerable, and effective dosage over 8 weeks. Most patients who switched from Xyrem to XYWAV (41/59; 69%) had no change in dosage from study entry to the stable dose period; 27% (16/59) had an increase in dosage, and 3% (2/59) had a decrease in dosage. Among patients whose dosage was changed, most changes were within one titration step (≤1.5 g). Patients not taking Xyrem at study entry were initiated at 4.5 g/night of XYWAV and titrated at a rate of 1 or 1.5 g/night/week to a tolerable dose of XYWAV. Patients taking an anticataplectic other than Xyrem were tapered off the non-Xyrem anticataplectic over 2 to 8 weeks. All patients continued to receive XYWAV only, for the treatment of cataplexy during the last 2 weeks of the OL OTTP.

CNS stimulants were allowed at entry, and approximately 59% of patients continued taking a stable dose of stimulant throughout the SDP and DB RWP.

The total nightly dose of XYWAV was administered in two equally divided doses in 90% (62/69) of patients. Unequal doses were administered in 10% (7/69) of patients treated with XYWAV.

The primary efficacy endpoint was the change in frequency of cataplexy attacks from the 2 weeks of the SDP to the 2 weeks of the DB RWP. The key secondary endpoint was the change in the Epworth Sleepiness Scale (ESS) score, as a measure of reduction in EDS from the end of the SDP to the end of the DB RWP.

Patients taking stable doses of XYWAV who discontinued XYWAV treatment and were randomized to placebo during the DB RWP experienced a significant worsening in the average weekly number of cataplexy attacks and in ESS score, compared with patients randomized to continue treatment with XYWAV (see Table 6).

Table 6: Mean and Median Number of Weekly Cataplexy Attacks and Epworth Sleepiness Scale (ESS)
 | Average Weekly Number of Cataplexy Attacks |  | ESS SCORE
 | Placebo (N=65) | XYWAV (N=69) | Placebo (N=65) | XYWAV (N=69)
Baseline (2 Weeks of the Stable Dose Period)
Mean (SD) | 7.2 (14.4) | 8.9 (16.8) | 12.6 (5.5) | 13.6 (5.3)
Median | 1.0 | 1.1 | 13.0 | 14.0
Change from Baseline (2 Weeks of the Stable Dose Period) to the 2 Weeks of the DB RWP |  |  | Change from End of Stable Dose Period to End of DB RWP
Mean (SD) | 11.5 (24.8) | 0.1 (5.8) | 3.0 (4.7) | 0.0 (2.9)
Median | 2.4 | 0.0 | 2.0 | 0.0
p-value | <0.0001 |  | <0.0001
DB RWP=Double‑blind Randomized-withdrawal Period; SD=standard deviation

14.2 Cataplexy and Excessive Daytime Sleepiness in Pediatric Narcolepsy

The effectiveness of XYWAV in pediatric patients is based upon a clinical study in patients treated with Xyrem, as described below, and additional pharmacokinetic information [see Use in Specific Populations (8.4)].

The effectiveness of Xyrem in the treatment of cataplexy and excessive daytime sleepiness in pediatric patients 7 years of age and older with narcolepsy was established in a double-blind, placebo-controlled, randomized-withdrawal study (NCT02221869). The study was conducted in 106 pediatric patients (median age: 12 years; range: 7 to 17 years) with a baseline history of at least 14 cataplexy attacks in a typical 2-week period prior to any treatment for narcolepsy symptoms. Of the 106 patients, 2 did not receive study drug and 63 patients were randomized 1:1 either to continued treatment with Xyrem or to placebo. Randomization to placebo was stopped early as the efficacy criterion was met at the pre-planned interim analysis.

Patients entered the study either taking a stable dosage of Xyrem or were Xyrem-naïve. CNS stimulants were allowed at entry, and approximately 50% of patients continued taking a stable dose of stimulant throughout the stable-dose and double-blind periods. Xyrem-naïve patients were initiated and titrated based on body weight over a period of up to 10 weeks. The total nightly dose was administered in two divided doses, with the first dose given at nighttime and the second given 2.5 to 4 hours later [see Dosage and Administration (2.2)]. Once a stable dosage of Xyrem had been achieved, these patients entered the 2-week stable-dose period; patients on a stable dosage of Xyrem at study entry remained on this dosage for 3 weeks prior to randomization. Efficacy was established at dosages ranging from 3 g to 9 g of Xyrem per night.

The primary efficacy measure was the change in frequency of cataplexy attacks. In addition, change in cataplexy severity was evaluated with the Clinical Global Impression of Change for cataplexy severity. The efficacy of Xyrem in the treatment of excessive daytime sleepiness in pediatric patients with narcolepsy was evaluated with the change in the Epworth Sleepiness Scale (Child and Adolescent) score. The Epworth Sleepiness Scale (Child and Adolescent) is a modified version of the scale used in the adult clinical trial described above. The overall change in narcolepsy condition was assessed by the Clinical Global Impression of Change for narcolepsy overall. Efficacy was assessed during or at the end of the 2-week double-blind treatment period, relative to the last 2 weeks or end of the stable-dose period (see Tables 7 and 8).

Pediatric patients taking stable dosages of Xyrem who discontinued Xyrem treatment and were randomized to placebo during the double-blind treatment period experienced a statistically significant increase in weekly cataplexy attacks compared with patients who were randomized to continue treatment with Xyrem. Patients randomized to receive placebo during the double-blind treatment period experienced a statistically significant worsening of EDS compared with patients randomized to continue receiving Xyrem (see Table 7).

Table 7: Number of Weekly Cataplexy Attacks and Epworth Sleepiness Scale (Child and Adolescent) Score
Treatment Group | Baseline*,† | Double-blind Treatment Period‡,§ | Median Change from Baseline | Comparison to Placebo (p-value¶)
Median Number of Cataplexy Attacks (attacks/week)
Placebo (n=32) | 4.7 | 21.3 | 12.7 | -
Xyrem (n=31) | 3.5 | 3.8 | 0.3 | <0.0001
Median Epworth Sleepiness Scale (Child and Adolescent) Score
Placebo (n=31**) | 11 | 12 | 3 | -
Xyrem (n=30**) | 8 | 9 | 0 | 0.0004
* For weekly number of cataplexy attacks, baseline value is calculated from the last 14 days of the stable-dose period.
† For Epworth Sleepiness Scale score, baseline value is collected at the end of stable-dose period.
‡ Weekly number of cataplexy attacks is calculated from all days within the double-blind treatment period.
§ For Epworth Sleepiness Scale, value is collected at the end of the double-blind treatment period.
¶ P-value from rank-based analysis of covariance (ANCOVA) with treatment as a factor and rank baseline value as a covariate.
** One patient in each of the treatment groups did not have baseline ESS score available and were not included in this analysis.

Patients randomized to receive placebo during the double-blind treatment period experienced a statistically significant worsening of cataplexy severity and narcolepsy overall according to the clinician’s assessment compared with patients randomized to continue receiving Xyrem (see Table 8).

Table 8: Clinical Global Impression of Change (CGIc) for Cataplexy Severity and Narcolepsy Overall
Worsened, %† | CGIc Cataplexy Severity* |  | CGIc Narcolepsy Overall*
Worsened, %† | Placebo (n=32) | Xyrem (n=29)‡ | Placebo (n=32) | Xyrem (n=29)‡
Much worse or very much worse | 66% | 17% | 59% | 10%
p-value§ | 0.0001 |  | <0.0001
* Responses indicate change of severity or symptoms relative to receiving Xyrem treatment at baseline.
† Percentages based on total number of observed values.
‡ Two patients randomized to Xyrem did not have the CGIc assessments completed and were excluded from the analysis.
§ P-value from Pearson’s chi-square test.

14.3 Idiopathic Hypersomnia (IH) in Adults

Efficacy of XYWAV for the treatment of IH in adult patients as a once or twice nightly regimen was established in a double-blind, placebo-controlled, randomized-withdrawal, study (Study 2, NCT03533114). Study 2 consisted of a minimum of 10‑week open‑label treatment titration and optimization period (OL OTTP), (with up to 4 additional weeks) to allow for an optimally effective and tolerable dose and regimen followed by a 2‑week stable dose period (SDP), a 2‑week double-blind, randomized withdrawal period (DB RWP), and a 24‑week open label safety extension period (OLE).

Study 2 enrolled 154 patients with idiopathic hypersomnia, 19 to 75 years of age. Of the 154 patients, 115 were evaluable for efficacy data and were randomized 1:1 to continue treatment with XYWAV or to placebo in the 2‑week DB RWP. In the safety population, overall, the median age was 39 years (range: 19 to 75). At baseline, 2% of patients were taking Xyrem only, 4% of patients were taking Xyrem and an additional stimulant or alerting agent, 54% of patients were not currently taking Xyrem but were taking a stimulant or alerting agent, and 41% were treatment naïve. CNS stimulants were allowed at entry, and approximately 57% of patients continued taking a stable dose of stimulant throughout the SDP and DB RWP.

The majority of subjects were female (71%), and most were white (81%) and not Hispanic or Latino (79%).

The XYWAV dosing regimen was initiated at the discretion of the investigator according to clinical presentation. Patients were considered for XYWAV once nightly if they reported difficulty awakening as a result of sleep inertia or long sleep time. Patients were considered for twice nightly dosing if they reported disrupted nighttime sleep or difficulty with sleep maintenance. For twice nightly regimens, doses were divided equally or unequally, with the first dose administered at bedtime and the second dose administered 2.5 to 4 hours later.

Based on clinical response during the OTTP, investigators were permitted to switch patients between twice nightly and once nightly dosing regimens. When patients were switched from a twice nightly to a once nightly dosing regimen, the total nightly dose was initially the same as the first dose of the twice nightly dosing regimen. When patients were switched from a once nightly to a twice nightly dosing regimen, the total nightly dose was no more than 1.5 g higher than the current dose, divided into two doses.

At the start of the DB RWP, 23% (27/115) of patients were taking XYWAV once nightly (median nightly dose 4.5 g), and 77% (88/115) of patients were taking XYWAV twice nightly (median nightly dose 7.5 g). There were no meaningful differences in demographics, baseline characteristics or disease severity between patients receiving XYWAV once nightly vs twice nightly.

The primary efficacy endpoint was the change in Epworth Sleepiness Scale (ESS) score, as a measure of reduction in EDS from the end of the SDP to the end of the DB RWP. The ESS is an 8-item self-reported questionnaire by which patients rate their perceived likelihood of falling asleep during usual daily life activities. Each of the 8 items on the ESS is rated from 0 (would never doze) to 3 (high chance of dozing), with a maximum score of 24. Key secondary efficacy endpoints included patient global impression of change (PGIc) and the Idiopathic Hypersomnia Severity Scale (IHSS), both assessed as a change from the end of the SDP to the end of the DB RWP. The IHSS is a 14-item self-reported questionnaire assessing the severity of IH symptoms of excessive sleepiness, prolonged sleep duration, cognitive impairment, and sleep inertia. Total scores can range from 0-50, with higher scores indicating a greater severity or frequency of symptoms.

Change in ESS

Patients in Study 2 taking stable doses of XYWAV who were withdrawn from XYWAV treatment and randomized to placebo during DB RWP experienced significant worsening in ESS score compared with patients randomized to continue treatment with XYWAV (p<0.0001) across all dosing regimens (see Table 9). These two treatment groups had comparable median ESS scores (Placebo=17; XYWAV=16) at entry into the OTTP.

Table 9: Median Change in Epworth Sleepiness Scale (ESS)
ESS Score
 | Placebo; (N=59) | XYWAV; (N=56)
Baseline End of 2-Week SDP
Median | 5.0 | 6.5
End of 2-Week DB RWP
Median | 14.0 | 7.0
Median Change from End of 2-Week SDP to End of 2-Week DB RWP
Median | 8.0 | 0.0
p-value | <0.0001
SDP=Stable Dose Period
DB RWP=Double-blind Randomized-withdrawal Period

PGIc

Patient Global Impression of change (PGIc) ratings showed that patients randomized to placebo experienced a worsening of symptoms of idiopathic hypersomnia overall compared with patients randomized to XYWAV (Table 10). The percentage of patients with worsening PGIc scores for IH overall (defined as scores of Minimally, Much Worse, or Very Much Worse) was greater for patients receiving placebo (88.1%) compared with patients receiving XYWAV (21.4%) (p<0.0001).

Table 10: PGIc* at End of the DB RWP†
 | PGIc* IH Overall
Worsened,% ‡† | Placebo (N=59) n (%) | XYWAV (N=56) n (%)
Proportion Worsened (minimally, much, or very much worse) | 52 (88.1) | 12 (21.4)
p‑value | <0.0001 | n/a
*PGIc is a 7‑point patient-reported scale by which patients rated their symptom change from “very much improved” to “very much worse.”
†DB RWP=Double‑blind Randomized-withdrawal Period.
‡At the end of the DB RWP/early termination visit, patients rated the change in their condition since the end of the Open-Label Stable-Dose Period.

IHSS

At end of DB RWP, patients randomized to placebo experienced a worsening in IHSS total score, compared to patients randomized to XYWAV (p<0.0001) (see Table 11). These two treatment groups had comparable median IHSS scores (Placebo=33; XYWAV=33) at entry into the OTTP.

Table 11: Median Changes in IHSS Total Score
Total Score
 | Placebo; (N=59) | XYWAV; (N=56)
Baseline End of 2-Week SDP
Median | 14.0 | 14.0
End of 2-Week DB RWP
Median | 29.0 | 16.0
Median Change from End of 2-Week SDP to End of 2-Week DB RWP
Median | 14.0 | 0.0
p-value | <0.0001
SDP=Stable Dose Period
DB RWP=Double‑blind Randomized-withdrawal Period

16 HOW SUPPLIED/STORAGE AND HANDLING

16.1 How Supplied

XYWAV is a clear to slightly opalescent oral solution. Each prescription includes at least one bottle of XYWAV with attached press in bottle adaptor, an oral measuring device (plastic syringe), and a Medication Guide. The pharmacy provides two empty containers with child-resistant caps with each XYWAV shipment.

Each amber bottle contains XYWAV oral solution at a concentration of 0.5 g/mL and has a child-resistant cap.

One 180 mL bottle: NDC 68727-150-01

16.2 Storage

Keep out of reach of children.

XYWAV should be stored between 20°C to 25°C (68°F to 77°F); excursions permitted between 15°C and 30°C (59°F and 86°F) (see USP Controlled Room Temperature).

Dispense in tight containers.

Solutions prepared following dilution should be consumed within 24 hours.

16.3 Handling and Disposal

XYWAV is a Schedule III drug under the Controlled Substances Act. XYWAV should be handled according to state and federal regulations. It is safe to dispose of XYWAV down the sanitary sewer.

17 PATIENT COUNSELING INFORMATION

Advise the patient and/or caregiver to read the FDA-approved patient labeling (Medication Guide and Instructions for Use).

Central Nervous System Depression

Inform patients and/or caregivers that XYWAV can cause central nervous system depression, including respiratory depression, hypotension, profound sedation, syncope, and death. Instruct patients not to engage in activities requiring mental alertness or motor coordination, including operating hazardous machinery, for at least 6 hours after taking XYWAV. Instruct patients and/or their caregivers to inform their healthcare providers of all the medications they take [see Warnings and Precautions (5.1)].

Abuse and Misuse

Inform patients and/or caregivers that the active ingredient of XYWAV is gamma-hydroxybutyrate (GHB), which is associated with serious adverse reactions with illicit use and abuse [see Warnings and Precautions (5.2)].

XYWAV and XYREM REMS

XYWAV is available only through a restricted program called the XYWAV and XYREM REMS [see Warnings and Precautions (5.3)]. Inform the patient and/or caregiver of the following notable requirements:

- XYWAV is dispensed only by the central pharmacy
- XYWAV will be dispensed and shipped only to patients enrolled in the XYWAV and XYREM REMS

XYWAV is available only from the central pharmacy participating in the program. Therefore, provide patients and/or caregivers with the telephone number and website for information on how to obtain the product.

Alcohol or Sedative Hypnotics

Advise patients and/or caregivers that alcohol and other sedative hypnotics should not be taken with XYWAV [see Contraindications (4)].

Sedation

Inform patients and/or caregivers that the patient is likely to fall asleep quickly after taking XYWAV (often within 5 and usually within 15 minutes), but the time it takes to fall asleep can vary from night to night. The sudden onset of sleep, including in a standing position or while rising from bed, has led to falls complicated by injuries, in some cases requiring hospitalization [see Adverse Reactions (6.2)]. Instruct patients and/or caregivers that the patient should remain in bed following ingestion of each dose. Instruct patients and/or caregivers that the patient should not take a subsequent nightly dose until at least 2.5 to 4 hours after the previous dose [see Dosage and Administration (2.4)].

Administration Instructions

Inform patients to administer XYWAV at least 2 hours after eating. Inform patients and/or caregivers of patients taking XYWAV twice nightly, that the total nightly dosage of XYWAV is divided into two doses [see Dosage and Administration (2.4)].

Inform patients if their nightly dose requires multiple draws. Instruct patients on how to perform the draws from the bottle.

Respiratory Depression and Sleep-Disordered Breathing

Inform patients that XYWAV may impair respiratory drive, especially in patients with compromised respiratory function, and may cause apnea [see Warnings and Precautions (5.4)].

Depression and Suicidality

Instruct patients and/or caregivers to contact a healthcare provider immediately if the patient develops depressed mood, markedly diminished interest or pleasure in usual activities, significant change in weight and/or appetite, psychomotor agitation or retardation, increased fatigue, feelings of guilt or worthlessness, slowed thinking or impaired concentration, or suicidal ideation [see Warnings and Precautions (5.5)].

Other Behavioral or Psychiatric Adverse Reactions

Inform patients and/or caregivers that XYWAV can cause behavioral or psychiatric adverse reactions, including confusion, anxiety, and psychosis. Instruct them to notify their healthcare provider if any of these types of symptoms occur [see Warnings and Precautions (5.6)].

Sleepwalking

Instruct patients and/or caregivers that XYWAV has been associated with sleepwalking and other behaviors during sleep, and to contact their healthcare provider if this occurs [see Warnings and Precautions (5.7)].

Distributed By:
Jazz Pharmaceuticals, Inc.
Palo Alto, CA 94306
Protected by U.S. Patent Nos. 8,591,922; 8,772,306; 8,901,173; 9,050,302; 9,132,107; 9,486,426; 9,555,017; 10,195,168; 10,213,400; 10,675,258; 10,864,181; 11,253,494; 11,554,102; and 11,426,373.

MEDICATION GUIDE
XYWAV® (ZYE wave)
(calcium, magnesium, potassium, and sodium oxybates)
oral solution, CIII

Read this Medication Guide carefully before you start or your child starts taking XYWAV, and each time you get or your child gets a refill. There may be new information. This information does not take the place of talking to your doctor about your or your child’s medical condition or treatment.

What is the most important information I should know about XYWAV?

- XYWAV is a central nervous system (CNS) depressant. Taking XYWAV with other CNS depressants, such as medicines used to make you or your child fall asleep, including opioid analgesics, benzodiazepines, sedating antidepressants, antipsychotics, sedating anti-epileptic medicines, general anesthetics, muscle relaxants, alcohol, or street drugs, may cause serious medical problems, including:
  - trouble breathing (respiratory depression)
  - low blood pressure (hypotension)
  - changes in alertness (drowsiness)
  - fainting (syncope)
  - death

Ask your doctor if you are not sure if you are, or your child is, taking a medicine listed above.

- XYWAV is a federal controlled substance (CIII). The active ingredient of XYWAV is a form of gamma-hydroxybutyrate (GHB) that is also a federal controlled substance (CI). Abuse of illegal GHB, either alone or with other CNS depressants, may cause serious medical problems, including:
  - seizure
  - trouble breathing (respiratory depression)
  - changes in alertness (drowsiness)
  - coma
  - death

Call your doctor right away if you have or your child has any of these serious side effects.

- Anyone who takes XYWAV should not do anything that requires them to be fully awake or is dangerous, including driving a car, using heavy machinery, or flying an airplane, for at least 6 hours after taking XYWAV. Those activities should not be done until you know how XYWAV affects you or your child.
- Keep XYWAV in a safe place to prevent abuse and misuse. Selling or giving away XYWAV may harm others and is against the law. Tell your doctor if you have ever abused or been dependent on alcohol, prescription medicines, or street drugs.
- Because of the risk of CNS depression, abuse, and misuse, XYWAV is available only by prescription, and filled through the central pharmacy in the XYWAV and XYREM REMS. You or your child must be enrolled in the XYWAV and XYREM REMS to receive XYWAV. For information on how to receive XYWAV, visit www.XYWAVXYREMREMS.com. Before you receive or your child receives XYWAV, your doctor or pharmacist will make sure that you understand how to take XYWAV safely and effectively. If you have any questions about XYWAV, ask your doctor or call the XYWAV and XYREM REMS at 1-866-997-3688.

What is XYWAV?

XYWAV is a prescription medicine used to treat:

- the following symptoms in people 7 years of age or older with narcolepsy:
  - sudden onset of weak or paralyzed muscles (cataplexy), or
  - excessive daytime sleepiness (EDS)
- idiopathic hypersomnia (IH) in adults

It is not known if XYWAV is safe and effective in children less than 7 years of age with narcolepsy.

It is not known if XYWAV is safe and effective in children with IH.

Do not take XYWAV if you or your child:

- takes other sleep medicines or sedatives (medicines that cause sleepiness)
- drinks alcohol
- has a rare problem called succinic semialdehyde dehydrogenase deficiency

Before taking XYWAV, tell your doctor about all medical conditions, including if you or your child:

- have a history of drug abuse.
- have short periods of not breathing while sleeping (sleep apnea).
- has trouble breathing or has lung problems. You or your child may have a higher chance of having serious breathing problems when taking XYWAV.
- have or had depression or has tried to harm yourself or themselves. You or your child should be watched carefully for new symptoms of depression.
- has or had behavior or other psychiatric problems such as:
  - anxiety
  - feeling more suspicious (paranoia)
  - acting aggressive
  - seeing or hearing things that are not real (hallucinations)
  - being out of touch with reality (psychosis)
  - agitation
- have liver problems.
- are pregnant or plan to become pregnant. It is not known if XYWAV can harm your unborn baby.
- are breastfeeding or plan to breastfeed. XYWAV passes into breast milk. You and your doctor should decide if you or your child will take XYWAV or breastfeed.

Tell your doctor about all the medicines you take or your child takes, including prescription and over-the-counter medicines, vitamins, and herbal supplements.

Especially, tell your doctor if you take or your child takes other medicines to help you or your child sleep (sedatives). Know the medicines you take or your child takes. Keep a list of them to show your doctor and pharmacist when you get or your child gets a new medicine.

How should I take or give XYWAV?

- Read the Instructions for Use at the end of this Medication Guide for detailed instructions on how to take XYWAV.
- Take or give XYWAV exactly as your doctor tells you to take or give it. Your doctor may change the dose or dosing routine if needed.
- Wait at least 2 hours after eating before taking or giving XYWAV.
- XYWAV can cause physical dependence and craving for the medicine when it is not taken as directed.
- Never change the dose without talking to your doctor.
- XYWAV can cause sleep very quickly without feeling drowsy. Some people fall asleep within 5 minutes and most fall asleep within 15 minutes. The time it takes to fall asleep might be different from night to night.
- Falling asleep quickly, including while standing or while getting up from the bed, has led to falls with injuries that have required some people to be hospitalized.
- XYWAV can be taken 1 time or 2 times a night as prescribed by your doctor.
- If you or your child have been prescribed XYWAV 2 times a night: divide the total nightly dose into 2 doses to be taken at bedtime and 2½ to 4 hours later.
  - Adults: Take the first XYWAV dose at bedtime while you are in bed and lie down immediately. Take the second XYWAV dose 2½ to 4 hours after the first XYWAV dose. You may want to set an alarm clock to make sure you wake up to take the second XYWAV dose. You should remain in bed after taking the first and second doses of XYWAV.
  - Children: Give the first XYWAV dose at bedtime or after an initial period of sleep, while your child is in bed and have them lie down immediately. Give the second XYWAV dose 2½ to 4 hours after the first XYWAV dose. You may want to set an alarm clock to make sure you wake up to give the second XYWAV dose. Your child should remain in bed after taking the first and second doses of XYWAV.
  - If you miss or your child misses the second XYWAV dose, skip that dose and do not take or give XYWAV again until the next night. Never take or give 2 XYWAV doses at 1 time.
- If you have been prescribed XYWAV 1 time a night: Take your XYWAV dose at bedtime while you are in bed and lie down immediately. You should remain in bed after taking XYWAV.
- If you take or your child takes too much XYWAV, call your doctor or go to the nearest hospital emergency room right away.

What are the possible side effects of XYWAV?

XYWAV can cause serious side effects, including:

- See “What is the most important information I should know about XYWAV?”
- breathing problems, including:
  - slower breathing.
  - trouble breathing.
  - short periods of not breathing while sleeping (sleep apnea). People who already have breathing or lung problems have a higher chance of having breathing problems when they take XYWAV.
- mental health problems, including:
  - confusion
  - seeing or hearing things that are not real (hallucinations)
  - unusual or disturbing thoughts (abnormal thinking)
  - feeling anxious or upset
  - depression
  - thoughts of killing yourself or trying to kill yourself
  - increased tiredness
  - feelings of guilt or worthlessness
  - difficulty concentrating

Call your doctor right away if you have or your child has symptoms of mental health problems, or a change in weight or appetite.

- sleepwalking. Sleepwalking can cause injuries. Call your doctor if you start or your child starts sleepwalking. Your doctor should check you or your child.

The most common side effects of XYWAV in adults with narcolepsy or IH include:

- nausea
- headache
- dizziness
- anxiety
- insomnia
- decreased appetite
- excessive sweating (hyperhidrosis)
- vomiting
- diarrhea
- dry mouth
- parasomnia (a sleep disorder that can include abnormal dreams, abnormal rapid eye movement (REM) sleep, sleep paralysis, sleep talking, sleep terror, sleep-related eating disorder, sleepwalking and other abnormal sleep-related events)
- somnolence
- fatigue
- tremor

The most common side effects of XYREM (which also contains oxybate like XYWAV) in children include:

- nausea
- bedwetting
- vomiting
- headache
- weight decrease
- decreased appetite
- dizziness
- sleepwalking

These are not all the possible side effects of XYWAV. For more information, ask your doctor or pharmacist.

Call your doctor for medical advice about side effects. You may report side effects to FDA at 1-800-FDA-1088.

How should I store XYWAV?

- Store XYWAV in the original bottle prior to mixing with water. After mixing with water, store XYWAV in the pharmacy containers with child-resistant caps provided by the pharmacy.
- Store XYWAV at room temperature between 68°F to 77°F (20°C to 25°C).
- XYWAV solution prepared after mixing with water should be taken within 24 hours.
- When you have finished using a XYWAV bottle:
  - empty any unused XYWAV down the sink drain.
  - cross out the label on the XYWAV bottle with a marker.
  - place the empty XYWAV bottle in the trash.

XYWAV comes in a child-resistant package.

Keep XYWAV and all medicines out of the reach of children and pets.

General information about the safe and effective use of XYWAV.

Medicines are sometimes prescribed for purposes other than those listed in a Medication Guide. Do not use XYWAV for a condition for which it was not prescribed. Do not give XYWAV to other people, even if they have the same symptoms. It may harm them.

You can ask your pharmacist or doctor for information about XYWAV that is written for health professionals.

What are the ingredients in XYWAV?
Active ingredients: calcium oxybate, magnesium oxybate, potassium oxybate, and sodium oxybate (gamma-hydroxybutyrate (GHB)).

Inactive ingredients: purified water and sucralose

Distributed By:
Jazz Pharmaceuticals, Inc.
Palo Alto, CA 94306

For more information, go to www.XYWAVXYREMREMS.com or call the XYWAV and XYREM REMS at 1-866-997-3688.

This Medication Guide has been approved by the U.S. Food and Drug Administration Revised: 7/2025

INSTRUCTIONS FOR USE
XYWAV® (ZYE wave)
(calcium, magnesium, potassium, and sodium oxybates)
oral solution, CIII

This Instructions for Use contains information on how to take XYWAV. Read this Instructions for Use carefully before you (or your child) start taking XYWAV and each time you (or your child) get a refill. There may be new information. This information does not take the place of talking to your doctor about your (or your child’s) medical condition or treatment.

Important Information:

- Your doctor and pharmacist will provide instructions to take XYWAV 2 times a night or 1 time a night.
  - For 2 times a night, you will need to split your (or your child’s) prescribed XYWAV dose into 2 separate pharmacy containers for mixing.
  - For 1 time a night, you will use the dosing syringe to draw up your prescribed XYWAV dose and empty the dose into 1 pharmacy container for mixing. You will only need 1 pharmacy container to prepare your dose.
- You (or your child) should take XYWAV while in bed. Lie down immediately after taking XYWAV and remain in bed afterwards.
- You will need to mix XYWAV with water before you take or give your child the dose.
- Safely store the prepared XYWAV doses and take within 24 hours after mixing. If the prepared dose was not taken within this time, throw the mixture away. See “Throwing away (disposing of) XYWAV” section below for instructions about how to safely throw away XYWAV.
- The pharmacy container(s) may be rinsed out with water and emptied into the sink drain.

Supplies you will need for mixing and taking (or giving your child) XYWAV. See Figure A:

- Bottle of XYWAV medicine
- Dosing syringe for measuring and dispensing the XYWAV dose
- Measuring cup that is able to measure about ¼ cup of water (not provided with the XYWAV shipment)
- 1 or 2 empty pharmacy containers with child-resistant caps for mixing, storing, and taking the XYWAV doses
- Alarm clock if you take XYWAV 2 times a night (not pictured)
- Medication Guide

Note: If you or your child are prescribed XYWAV 2 times a night, see the instructions for 2 times a night dosing. If you are prescribed XYWAV 1 time a night, see the instructions for 1 time a night dosing.

2 times a night dosing

Step 1. Setup

- Take the XYWAV bottle, syringe, and pharmacy containers out of the shipping box.
- Take the syringe out of the plastic wrapper. Use only the syringe provided with the XYWAV prescription.
- Fill a measuring cup (not provided) with about ¼ cup of water available for mixing your (or your child’s) dose.

- Make sure the pharmacy containers are empty.
- Open both pharmacy containers by holding the tab under the cap and turning counterclockwise (to the left). See Figure B

Figure B

- Remove the tamper evident band by pulling at the perforations and then remove the child-resistant bottle cap from the XYWAV bottle by pushing down while turning the cap counterclockwise. See Figure C

Figure C

Step 2. Prepare the first XYWAV dose (prepare before bedtime)

Place the XYWAV bottle on a hard, flat surface and grip the bottle with one hand. Firmly press the syringe into the center opening of the bottle with the other hand. See Figure D

Figure D

Pull back on the plunger until the medicine flows into the syringe and the liquid level is lined up with the marking on the syringe that matches your or your child’s dose. See Figure E

Figure E

Note: The XYWAV medicine will not flow into the syringe unless you keep the bottle upright.

Figure F shows an example of drawing up a 2.25 g dose of XYWAV. Figure G shows an example if an air space forms when drawing up the medicine.

Note: If an air space forms between the plunger and the liquid when drawing up the medicine, line up the liquid level with the marking on the syringe that matches your (or your child’s) dose. See Figure G

Figure F Figure G

- After you draw up the first divided dose, remove the syringe from the opening of the XYWAV bottle.
- Empty all of the medicine from the syringe into one of the provided empty pharmacy containers by pushing down on the plunger until it stops. See Figure H

Figure H

- Using a measuring cup, pour about ¼ cup of water into the pharmacy container. Be careful to add only water to the pharmacy container and not more XYWAV.
- All shipped bottles of XYWAV contain the concentrated medicine. Water for mixing the medicine is not provided in the shipment.
- After mixing the medicine and water in the provided pharmacy container, place the child-resistant cap on the filled pharmacy container and turn the cap clockwise (to the right) until it clicks and locks into its child-resistant position. See Figure I.
- Caution: the pharmacy container cap is reversible with a non-child resistant side. See Figure J. Make sure the child-resistant side of the cap is used to prevent access to the medicine by children.

Cap shown in child-resistant position.

Figure I

Figure J

Step 3. Prepare the second XYWAV dose (prepare before bedtime)

- Repeat Step 2 drawing up the amount of medicine prescribed for your (or your child’s) second dose:
  - emptying the syringe into the second pharmacy container
  - adding about ¼ cup of water and
  - closing the pharmacy container

Step 4. Store the prepared XYWAV doses

- Put the cap back on the XYWAV bottle and store the XYWAV bottle and both prepared doses in a safe and secure place. Store in a locked place if needed.
- Keep the XYWAV bottle and both prepared XYWAV doses out of the reach of children and pets.
- Rinse the syringe out with water and squirt the liquid into the sink drain by pushing down on the plunger until it stops.

Step 5. Take or give the first XYWAV dose

- At bedtime, and before you take (or give) the first XYWAV dose, put the second XYWAV dose in a safe place. Caregivers should make sure all XYWAV doses are kept in a safe place until given. You may want to set an alarm clock for 2½ to 4 hours later to make sure you wake up to take (or give) the second dose.
- When it is time to take (or give) the first XYWAV dose, remove the cap from the pharmacy container by pressing down on the child-resistant locking tab and turning the cap counterclockwise.
- Drink (or have your child drink) all of the first XYWAV dose while sitting in bed. Put the cap back on the first pharmacy container and immediately lie down to sleep (or have your child lie down to sleep).
- You (or your child) should fall asleep soon. Some people fall asleep within 5 minutes and most fall asleep within 15 minutes. Some patients take less time to fall asleep, and some take more time. The time it takes you (or your child) to fall asleep might be different from night to night.

Step 6. Take or give the second XYWAV dose

- When you wake up 2½ to 4 hours later for your (or your child’s) second dose of XYWAV, take the cap off the second pharmacy container.
- If you (or your child) wake up before the alarm and it has been at least 2½ hours since the first XYWAV dose, turn off the alarm and take (or give your child) the second XYWAV dose.
- Drink (or have your child drink) all of the second XYWAV dose while sitting in bed. Put the cap back on the second pharmacy container and immediately lie down (or have your child lie down) to continue sleeping.

1 time a night dosing
for use in adults with idiopathic hypersomnia

Step 1. Setup

- Take the XYWAV bottle, syringe, and 1 pharmacy container out of the shipping box.
- Take the syringe out of the plastic wrapper. Use only the syringe provided with the XYWAV prescription.
- Fill a measuring cup (not provided) with about ¼ cup of water available for mixing with your dose.

- Make sure the pharmacy container is empty.
- Open the pharmacy container by holding the tab under the cap and turning counterclockwise (to the left). See Figure B

Figure B

- Remove the tamper evident band by pulling at the perforations and then remove the child-resistant bottle cap from the XYWAV bottle by pushing down while turning the cap counterclockwise. See Figure C

Figure C

Step 2. Prepare the XYWAV dose (prepare before bedtime)

Place the XYWAV bottle on a hard, flat surface and grip the bottle with one hand. Firmly press the syringe into the center opening of the bottle with the other hand. See Figure D

Figure D

Pull back on the plunger until the medicine flows into the syringe and the liquid level is lined up with the marking on the syringe that matches your dose. You may need to draw up the medicine a second time to make up your total prescribed dose.

See Figure E

Figure E

Note: The XYWAV medicine will not flow into the syringe unless you keep the bottle upright.

Figure F shows an example of drawing up 2.25 g of XYWAV. Figure G shows an example if an air space forms when drawing up the medicine.

Note: If an air space forms between the plunger and the liquid when drawing up the medicine, line up the liquid level with the marking on the syringe that matches your dose. See Figure G

Figure F Figure G

- After you draw up the medicine, remove the syringe from the opening of the XYWAV bottle.
- Empty all of the medicine from the syringe into a single provided empty pharmacy container by pushing down on the plunger until it stops. See Figure H
- For doses requiring 2 draws from the XYWAV bottle, empty the second draw into the same pharmacy container.

Figure H

- After you finish adding your XYWAV dose to the pharmacy container, use a measuring cup to pour about ¼ cup of water into the pharmacy container. Be careful to add only water to the pharmacy container and not more XYWAV.
- All shipped bottles of XYWAV contain the concentrated medicine. Water for mixing the medicine is not provided in the shipment.
- After mixing the medicine and water in the provided pharmacy container, place the child-resistant cap on the filled pharmacy container and turn the cap clockwise (to the right) until it clicks and locks into its child-resistant position. See Figure I.
- Caution: the pharmacy container cap is reversible with a non-child resistant side. See Figure J. Make sure the child-resistant side of the cap is used to prevent access to the medicine by children.

Cap shown in child-resistant position.

Figure I

Figure J

Step 3. Store the prepared XYWAV dose

- Put the cap back on the XYWAV bottle and store the XYWAV bottle and the prepared dose in a safe and secure place. Store in a locked place if needed.
- Keep the XYWAV bottle and the prepared XYWAV dose out of the reach of children and pets.
- Rinse the syringe out with water and squirt the liquid into the sink drain by pushing down on the plunger until it stops.

Step 4. Take the XYWAV dose

- Make sure the XYWAV dose is kept in a safe place until taken.
- When it is time to take the XYWAV dose, remove the cap from the pharmacy container by pressing down on the child-resistant locking tab and turning the cap counterclockwise.
- Drink all of the XYWAV dose while sitting in bed. Put the cap back on the pharmacy container and immediately lie down to sleep.
- You should fall asleep soon. Some people fall asleep within 5 minutes and most fall asleep within 15 minutes. Some patients take less time to fall asleep, and some take more time. The time it takes you to fall asleep might be different from night to night.

How should I store XYWAV?

- Store XYWAV in the original bottle prior to mixing with water. After mixing, store XYWAV in the pharmacy containers provided by the pharmacy. The cap on the original bottle is child-resistant. The pharmacy container cap is child‑resistant only when the child-resistant side of the cap is used.
- Store XYWAV at room temperature between 68°F to 77°F (20°C to 25°C).
- XYWAV solution prepared after mixing with water should be taken within 24 hours or emptied down the sink drain.

Throwing away (disposing of) XYWAV

- When you have finished using a XYWAV bottle:
  - empty any unused XYWAV down the sink drain
  - cross out the label on the XYWAV bottle with a marker (not provided with the XYWAV shipment)
  - place the empty XYWAV bottle in the trash
- Keep XYWAV and all medicines out of the reach of children and pets.

Distributed By:
Jazz Pharmaceuticals, Inc.
Palo Alto, CA 94306

This Instructions for Use has been approved by the U.S. Food and Drug Administration. Revised: 7/2025